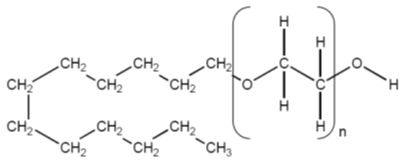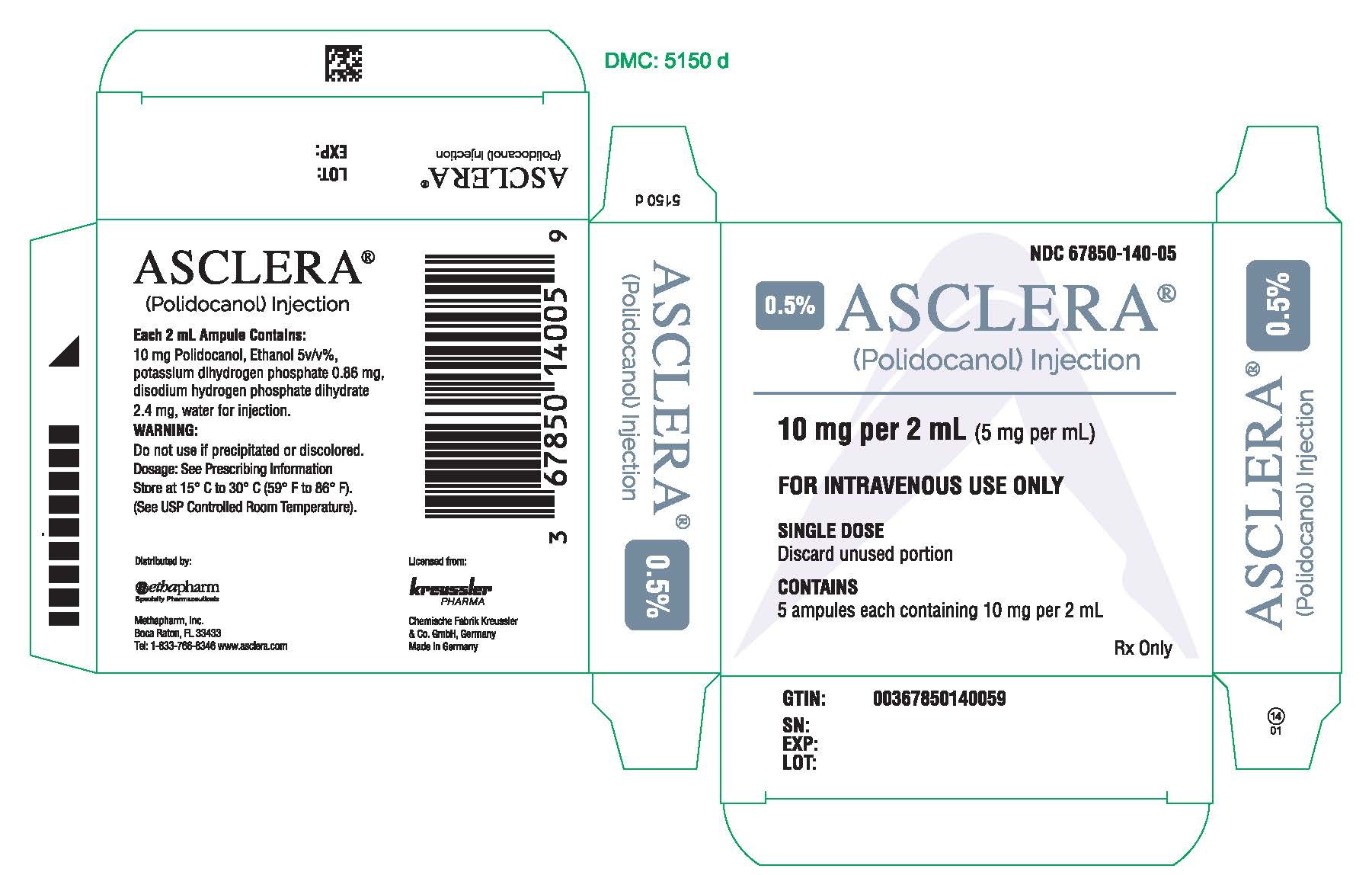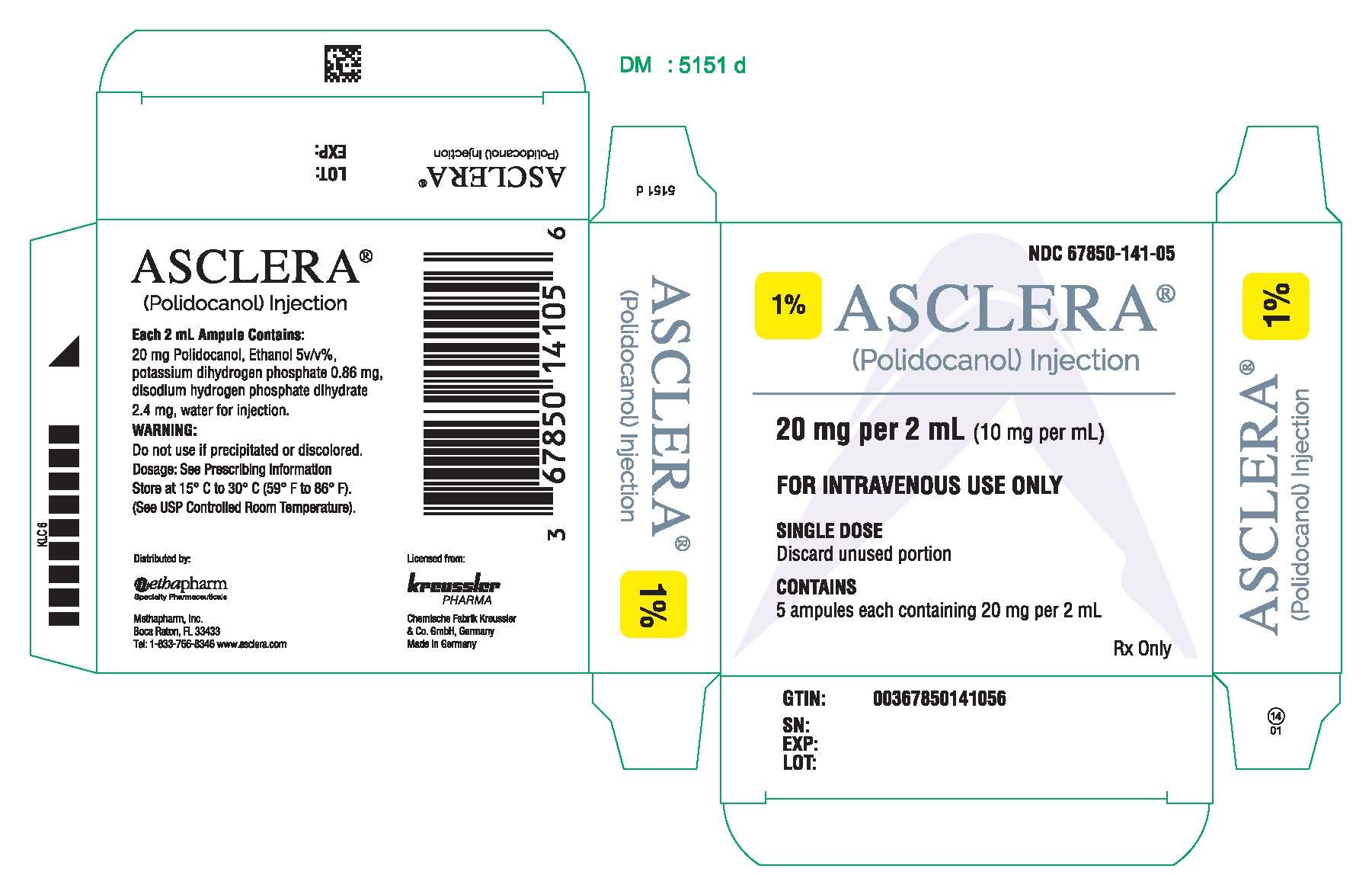 DRUG LABEL: Asclera
NDC: 67850-141 | Form: INJECTION, SOLUTION
Manufacturer: Methapharm, Inc
Category: prescription | Type: HUMAN PRESCRIPTION DRUG LABEL
Date: 20250716

ACTIVE INGREDIENTS: POLIDOCANOL 0.01000 g/1 mL
INACTIVE INGREDIENTS: ALCOHOL 0.04200 g/1 mL; MONOBASIC POTASSIUM PHOSPHATE 0.00085 g/1 mL; SODIUM PHOSPHATE, DIBASIC, UNSPECIFIED FORM 0.00240 g/1 mL; WATER 0.93875 g/1 mL

HIGHLIGHTS OF PRESCRIBING INFORMATION

These highlights do not include all the information needed to use Asclera® Injection safely and effectively. See full prescribing information for Asclera.
Asclera (polidocanol) Injection, for intravenous use Initial U.S. Approval: 2010

1 INDICATIONS AND USAGE

Asclera (polidocanol) is a sclerosing agent indicated to sclerose uncomplicated spider veins (varicose veins ≤1 mm in diameter) and uncomplicated reticular veins (varicose veins 1 to 3 mm in diameter) in the lower extremity. Asclera has not been studied in varicose veins more than 3mm in diameter. (1)

2 DOSAGE AND ADMINISTRATION

For intravenous use only. Solution strength and the volume injected depend on the size and extent of the varicose veins. Extensive varicosities may require multiple treatment sessions. (2)

Spider veins (varicose veins ≤1 mm in diameter): Use Asclera 0.5%. (2)

Reticular veins (varicose veins 1 to 3 mm in diameter): Use Asclera 1%. (2)

Use 0.1 to 0.3 mL for each injection into each varicose vein. The maximum recommended volume per treatment session is 10 mL. (2)

3 DOSAGE FORMS AND STRENGTHS

0.5% and 1% solution in 2 mL glass ampules. (3)

4 CONTRAINDICATIONS

Known allergies to polidocanol. (4)

Patients with acute thromboembolic diseases. (4)

5 WARNINGS AND PRECAUTIONS

- Be prepared to treat anaphylaxis. (5.1)
- Venous Thrombosis and Pulmonary Embolism. (5.2)
- Arterial Embolism. (5.3)
- Tissue ischemia and necrosis: Do not inject intra-arterially. (5.4)

6 ADVERSE REACTIONS

The most common adverse reactions occurring at least 3% more frequently than on placebo are mild local reactions at the site of injection. (6)

To report SUSPECTED ADVERSE REACTIONS, contact Methapharm at 1-866-701-4636 or
medinfo@methapharm.com or FDA at 1-800-FDA-1088 or www.fda.gov/medwatch.

FULL PRESCRIBING INFORMATION

1 INDICATIONS AND USAGE

Asclera® (polidocanol) is indicated to sclerose uncomplicated spider veins (varicose veins ≤1 mm in diameter) and uncomplicated reticular veins (varicose veins 1 to 3 mm in diameter) in the lower extremity. Asclera has not been studied in varicose veins more than 3 mm in diameter.

2 DOSAGE AND ADMINISTRATION

For intravenous use only. Parenteral drug products should be inspected visually for particulate matter and discoloration prior to administration, whenever solution and container permit. Do not use if particulate matter is seen or if the contents of the vial are discolored or if the vial is damaged in any way.

For spider veins (varicose veins ≤1 mm in diameter), use Asclera 0.5%. For reticular veins (varicose veins 1 to 3 mm in diameter), use Asclera 1%. Use 0.1 to 0.3 mL per injection and no more than 10 mL per session.

Use a syringe (glass or plastic) with a fine needle (typically, 26- or 30-gauge). Insert the needle tangentially into the vein and inject the solution slowly while the needle is still in the vein. Apply only gentle pressure during injection to prevent vein rupture. After the needle has been removed and the injection site has been covered, apply compression in the form of a stocking or bandage. After the treatment session, encourage the patient to walk for 15 to 20 minutes. Keep the patient under observation to detect any anaphylactic or allergic reaction [see Warnings and Precautions (5.3)].

Maintain compression for 2 to 3 days after treatment of spider veins and for 5 to 7 days for reticular veins. For extensive varicosities, longer compression treatment with compression bandages or a gradient compression stocking of a higher compression class is recommended. Post-treatment compression is necessary to reduce the risk of deep vein thrombosis.

Repeat treatments may be necessary if the extent of the varicose veins requires more than 10 mL. These treatments should be separated by 1 to 2 weeks.

Small intravaricose thrombi that develop may be removed by microthrombectomy.

3 DOSAGE FORMS AND STRENGTHS

Asclera (polidocanol) is an injection for intravenous use and is available as follows:

• 0.5% [10 mg/2 mL (5 mg/mL)] solution in 2 mL single-dose glass ampule
• 1% [20 mg/2 mL (10 mg/mL)] solution in 2 mL single-dose glass ampule

4 CONTRAINDICATIONS

Asclera is contraindicated for patients with known allergy to polidocanol and patients with acute thromboembolic diseases.

5 WARNINGS AND PRECAUTIONS

5.1 Anaphylaxis

Severe allergic reactions have been reported following polidocanol use, including anaphylactic reactions, some of them fatal. Severe reactions are more frequent with use of larger volumes (> 3 mL). Minimize the dose of polidocanol. Be prepared to treat anaphylaxis appropriately.

Severe adverse local effects, including tissue necrosis, may occur following extravasation; therefore, take care in intravenous needle placement and use the smallest effective volume at each injection.

After the injection session is completed, apply compression with a stocking or bandage, and have the patient walk for 15-20 minutes. Keep the patient under supervision during this period to treat any anaphylactic or allergic reaction [see Dosage and Administration (2)].

5.2 Venous Thrombosis and Pulmonary Embolism

Asclera can cause venous thrombosis and subsequent pulmonary embolism or other thrombotic events. Follow administration instructions closely and monitor for signs of venous thrombosis after treatment. Patients with reduced mobility, history of deep vein thrombosis or pulmonary embolism, or recent (within 3 months) major surgery, prolonged hospitalization or pregnancy are at increased risk for developing thrombosis.

5.3 Arterial Embolism

Stroke, transient ischemic attack, myocardial infarction, and impaired cardiac function have been reported in close temporal relationship with polidocanol administration. These events may be caused by air embolism when using the product foamed with room air (high nitrogen concentration) or thromboembolism. The safety and efficacy of polidocanol foamed with room air has not been established and its use should be avoided.

5.4 Tissue Ischemia and Necrosis

Intra-arterial injection or extravasation of polidocanol can cause severe necrosis, ischemia or gangrene. Take care in intravenous needle placement and use the smallest effective volume at each injection site. After the injection session is completed, apply compression with a stocking or bandage and have patients walk for 15-20 minutes. If intra-arterial injection of polidocanol occurs, consult a vascular surgeon immediately.

6 ADVERSE REACTIONS

6.1 Clinical Study Experience

Because clinical trials are conducted under widely varying conditions, adverse reaction rates observed in the clinical trials of a drug cannot be directly compared to rates in the clinical trials of another drug and may not reflect the rates observed in practice.

In 5 controlled randomized clinical trials, Asclera has been administered to 401 patients with small or very small varicose veins (reticular and spider veins) and compared with another sclerosing agent and with placebo. Patients were 18 to 70 years old. The patient population was predominately female and consisted of Caucasian and Asian patients.

Table 1 shows adverse events more common with Asclera or sodium tetradecyl sulfate (STS) 1% than with placebo by at least 3% in the placebo-controlled EASI study [see Clinical Studies (14)]. All of these were injection site reactions and most were mild.

Table 1: Adverse Reactions in EASI-study
 | ASCLERA (180 patients) | STS 1% (105 patients) | Placebo (53 patients)
Injection site haematoma | 42% | 65% | 19%
Injection site irritation | 41% | 73% | 30%
Injection site discoloration | 38% | 74% | 4%
Injection site pain | 24% | 31% | 9%
Injection site pruritus | 19% | 27% | 4%
Injection site warmth | 16% | 21% | 6%
Neovascularisation | 8% | 20% | 4%
Injection site thrombosis | 6% | 1% | 0%

Ultrasound examinations at one week (±3 days) and 12 weeks (±2 weeks) after treatment did not reveal deep vein thrombosis in any treatment group.

6.2 Post-marketing Safety Experience

The following adverse reactions have been reported during use of polidocanol in world-wide experience. Because these reactions are reported voluntarily from a population of uncertain size and without a control group, it is not possible to estimate their frequency reliably or to establish a causal relationship to drug exposure.

Immune system disorders: Anaphylactic shock, angioedema, urticaria generalized, asthma

Nervous system disorders: Cerebrovascular accident, migraine, paresthesia (local), loss of consciousness, confusional state, dizziness

Cardiac disorders: Cardiac arrest, palpitations

Vascular disorders: Deep vein thrombosis, pulmonary embolism, syncope vasovagal, circulatory collapse, vasculitis

Respiratory, thoracic and mediastinal disorders: Dyspnea

Skin and subcutaneous tissue disorders: Skin hyperpigmentation, dermatitis allergic, hypertrichosis (in the area of sclerotherapy)

General disorders and injection site conditions: Injection site necrosis, pyrexia, hot flush

Injury, poisoning and procedural complications: Nerve injury

7 DRUG INTERACTIONS

No drug-drug interactions have been studied with Asclera.

8 USE IN SPECIFIC POPULATIONS

8.1 Pregnancy

Risk Summary

The available data from case reports on use of polidocanol-containing products, including ASCLERA, in pregnant women have not identified any drug-associated risk for major birth defects, miscarriage, or adverse maternal or fetal outcomes. Although none of these risks have been identified, there is minimal benefit in treating uncomplicated spider veins and reticular veins in the lower extremity during pregnancy and lower extremity varicosities that develop during pregnancy as they may spontaneously regress postpartum. The animal reproduction studies were conducted in a manner to achieve systemic exposure, while the intended clinical use is local exposure at the injection site with minimal to no systemic exposure; therefore, these data are not relevant to the intended clinical use (see Data).

The estimated background risk of major birth defects and miscarriage for the indicated population is unknown. All pregnancies have a background risk of birth defect, loss, or other adverse outcomes. In the U.S. general population, the estimated background risk of major birth defects and miscarriage in clinically recognized pregnancies is 2 to 4% and 15 to 20%, respectively.

Data

Animal Data

Developmental reproductive toxicity testing was performed in rats and rabbits with intravenous administration. Polidocanol induced maternal and fetal toxicity in rabbits, including reduced mean fetal weight and reduced fetal survival, when administered during gestation days 6-20 at doses of 4 and 10 mg/kg, but it did not cause skeletal or visceral abnormalities. No adverse maternal or fetal effects were observed in rabbits at a dose of 2 mg/kg. No evidence of teratogenicity or fetal toxicity was observed in rats dosed during gestation days 6-17 with doses up to 10 mg/kg. Polidocanol did not affect the ability of rats to deliver and rear pups when administered intermittently by intravenous injection from gestation day 17 to post-partum day 21 at doses up to 10 mg/kg.

These studies were conducted in a manner to achieve systemic exposure, while the intended clinical use is local exposure at the injection site with minimal to no systemic exposure; therefore, these data are not relevant to the intended clinical use.

8.2 Lactation

Risk Summary

There are no data on the presence of polidocanol in human milk, the effects on the breastfed infant, or the effects on milk production. A lactating woman may consider interrupting breastfeeding and pumping and discarding breast milk up to 8 hours after ASCLERA administration in order to minimize exposure to a breastfed infant.

8.4 Pediatric Use

The safety and effectiveness of Asclera in pediatric patients have not been established.

8.5 Geriatric Use

Clinical studies of Asclera did not include sufficient numbers of subjects aged 65 and over to determine whether they respond differently from younger subjects.

10 OVERDOSAGE

Overdose may result in a higher incidence of localized reactions such as necrosis.

11 DESCRIPTION

Asclera is a sterile, nonpyrogenic, and colorless to faintly greenish-yellow solution of polidocanol for intravenous use as a sclerosing agent.

The active ingredient, polidocanol is a non-ionic detergent, consisting of two components, a polar hydrophilic (dodecyl alcohol) and an apolar hydrophobic (polyethylene oxide) chain. Polidocanol has the following structural formula:

C12H25(OCH2CH2)nOH Polyethylene glycol monododecyl ether Mean extent of polymerization (n) : Approximately 9 Mean molecular weight : Approximately 600

Each mL contains 5 mg (0.5%) or 10 mg (1.0%) polidocanol in water for injection with 5% (v/v) ethanol at pH 6.5-8.0; disodium hydrogen phosphate dihydrate (1.2 mg), potassium dihydrogen phosphate (0.43 mg).

12 CLINICAL PHARMACOLOGY

12.1 Mechanism of Action

The active ingredient of Asclera is polidocanol.

Polidocanol is a sclerosing agent that locally damages the endothelium of blood vessels. When injected intravenously, polidocanol induces endothelial damage. Platelets then aggregate at the site of damage and attach to the venous wall. Eventually, a dense network of platelets, cellular debris, and fibrin occludes the vessel. Finally, the occluded vein is replaced with connective fibrous tissue.

12.2 Pharmacodynamics

Polidocanol has a concentration- and volume-dependent damaging effect on the endothelium of blood vessels.

12.3 Pharmacokinetics

During the major effectiveness study (EASI-trial), scheduled blood samples were taken from a sub-group of 22 patients to measure plasma levels of polidocanol after Asclera treatment of spider and reticular veins. Low systemic blood levels of polidocanol were seen in some patients.

The mean t1/2 of polidocanol in 4 patients with evaluable data receiving 4.5 -18.0 mg was 1.5 h.

13 NONCLINICAL TOXICOLOGY

13.1 Carcinogenesis, Mutagenesis, Impairment of Fertility

Long-term studies to evaluate carcinogenic potential have not been conducted with polidocanol. Polidocanol was negative in bacterial reverse mutation assays in Salmonella and E. coli, and in a micronucleus assay conducted in mice. Polidocanol induced numerical chromosomal aberrations in cultured newborn Chinese hamster lung fibroblasts in the absence of metabolic activation.

Polidocanol did not affect reproductive performance (fertility) of rats when administered intermittently at dosages up to 10 mg/kg (approximately equal to the maximum human dose on the basis of body surface area).

14 CLINICAL STUDIES

Asclera was evaluated in a multicenter, randomized, double-blind, placebo- and comparator-controlled trial (EASI-study) in patients with spider or reticular varicose veins. A total of 338 patients were treated with Asclera [0.5% for spider veins (n=94), 1% for reticular veins (n=86)], sodium tetradecyl sulfate (STS) 1% (n=105), or placebo (0.9% isotonic saline solution) (n=53) for either spider or reticular veins. Patients were predominately female, ranging in age from 19 to 70 years. All of them received an intravenous injection in the first treatment session; repeat injections were given three and six weeks later if the previous injection was evaluated as unsuccessful (defined as 1, 2 or 3 on a 5-point scale, see below). Patients returned at 12 and 26 weeks after the last injection for final assessments.

The primary effectiveness endpoint was improvement of veins judged by a blinded panel. Digital images of the selected treatment area were taken prior to injection, compared with those taken at 12 weeks post-treatment, and rated on a 5-point scale (1 = worse than before, 2 = same as before, 3 = moderate improvement, 4 = good improvement, 5 = complete treatment success); results are shown in Table 2.

Table 2: Improvement of veins in digital photographs after 12 weeks and 26 weeks
Treatment Group | Polidocanol (n=155) | STS (n=105) | Placebo (n=53)
Digital Photograph Scores at 12 weeks
Mean ± SD | 4.5 [p <0.0001 compared to placebo (Wilcoxon-Mann-Whitney test)] ± 0.7 | 4.5± 0.7 | 2.2 ± 0.7
Digital Photograph Scores at 26 weeks
Mean ± SD | 4.5 ± 0.7 | 4.5± 0.8 | 2.2 ± 0.7

The secondary efficacy criterion was the rate of treatment success, pre-defined as a score of 4 or 5 with patients scoring 1, 2, or 3 considered treatment failures; results are shown in Table 3.

Table 3: Treatment success rates at 12 weeks and 26 weeks
Treatment Success [Treatment success: Yes= Grade 4 to 5, No= Grade 1 to 3; derived from median of evaluation;] | Polidocanol (n=155) | STS (n=105) | Placebo (n=53)
At 12 weeks (Visit 4)
Yes | 95% [p<0.0001 compared to placebo.] | 92% | 8%
No | 5% | 8% | 92%
Missing | 0.6% | 0% | 0%
At 26 weeks (Visit 5)
Yes | 95% | 91% | 6%
No | 5% | 9% | 94%

At 12 and 26 weeks, patients' judgement of the results was assessed by showing them the digital images of their treatment area taken at baseline and asking them to rate their satisfaction with their treatment using a verbal rating scale (1 = very unsatisfied; 2 = somewhat unsatisfied; 3 = slightly satisfied; 4 = satisfied and 5 = very satisfied); results are shown in Table 4.

Table 4: Patient satisfaction after 12 weeks and 26 weeks
Polidocanol (N=155) |  | STS (N=105) | Placebo (N=53)
Patient satisfaction with treatment after 12 weeks (Visit 4)
Satisfied or very satisfied | 87% [p <0.0001 compared to STS and placebo] | 64% | 14%
Patient satisfaction with treatment after 26 weeks (Visit 5)
Satisfied or very satisfied | 84% | 63% | 16%

16 HOW SUPPLIED/STORAGE AND HANDLING

Asclera (polidocanol) injection is a colorless to faintly greenish-yellow solution supplied in single-dose, sterile, preservative free ampules in the following packages:

NDC 67850-140-05 Five 0.5 % ampules [10 mg/2 mL (5 mg/mL)]
NDC 67850-141-05 Five 1 % ampules [20 mg/2 mL (10 mg/mL)]

Each ampule is intended for immediate use in a single patient. Each unopened ampule is stable up to three years.

STORAGE AND HANDLING

Store at 15°C to 30°C; (59°F to 86°F).

17 PATIENT COUNSELING INFORMATION

Advise the patient to wear compression stockings or support hose on the treated legs continuously for 2 to 3 days and for 2 to 3 weeks during the daytime. Compression stockings or support hose should be thigh or knee high depending upon the area treated in order to provide adequate coverage.

Advise the patient to walk for 15 to 20 minutes immediately after the procedure and daily for the next few days.

For two to three days following treatment, advise the patient to avoid heavy exercise, sunbathing, long plane flights, and hot baths or sauna.

Distributed by:

Methapharm, Inc.
Boca Raton, FL 33433
Tel: 1-833-766-8346
www.asclera.com

Manufactured by:
Chemische Fabrik Kreussler & Co. GmbH

65203 Wiesbaden GERMANY

Asclera is a registered trademark of Chemische Fabrik Kreussler & Co. GmbH, 65203 Wiesbaden, GERMANY

PRINCIPAL DISPLAY PANEL - 20 mg Ampule Carton

NDC 67850-141-05

ASCLERA®
(polidocanol) Injection

20 mg per 2 mL
(10 mg per mL)

1%

For Intravenous Use Only
Rx Only
Single use: Discard unused portion
Contains:
5 ampules each containing 20 mg per 2 mL

PRINCIPAL DISPLAY PANEL - 10 mg Ampule Carton

NDC 67850-140-05

ASCLERA®
(polidocanol) Injection

10 mg per 2 mL
(5 mg per mL)

0.5%

For Intravenous Use Only
Rx Only
Single use: Discard unused portion
Contains:
5 ampules each containing 10 mg per 2 mL